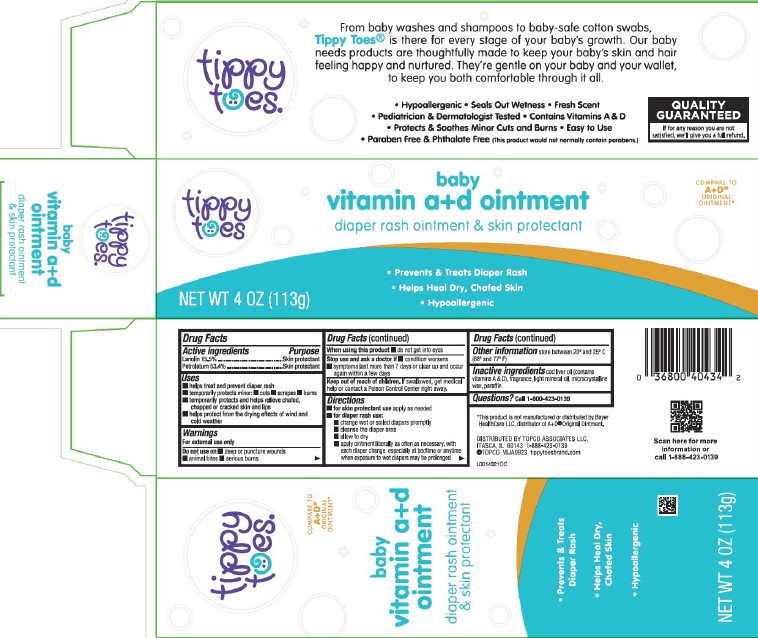 DRUG LABEL: Vitamin A D
NDC: 36800-017 | Form: OINTMENT
Manufacturer: Topco Associates LLC
Category: otc | Type: HUMAN OTC DRUG LABEL
Date: 20260213

ACTIVE INGREDIENTS: LANOLIN 155 mg/1 g; PETROLATUM 534 mg/1 g
INACTIVE INGREDIENTS: LIGHT MINERAL OIL; MICROCRYSTALLINE WAX; PARAFFIN; COD LIVER OIL

Tippy Toes 013.000/013AA-AB
Vitamin A&D Ointment

Active ingredients

Lanolin 15.5%

Petrolatum 53.4%

Purpose

Skin protectant

Uses

- helps treat and prevent diaper rash
- temporarily protects minor:
- cuts
- scrapes
- burns
- temporarily protects and helps relieve chafed, chapped or cracked skin and lips
- helps protect from the drying effects of wind and cold weather

Warnings

For external use only

Do not use on

- deep or puncture wounds
- animal bites
- serious burns

When using this product

- do not get into eyes

Stop use and ask a doctor if

- condition worsens
- symptoms last more than 7 days or clear up and occur again within a few days

Keep out of reach of children.

If swallowed, get medical help or contact a Poison Control Center right away.

Directions

- for skin protectant use apply as needed
- for diaper rash use:
- change wet or soilded diapers promptly
- cleanse the diaper area
- allow to dry
- apply ointment liberally as often as necessry, with each diaper change, especially at bedtime or anytime when exposure to wet diapers may be prolonged

Other information

store between 20º and 25ºC (68º and 77ºF)

Inactive ingredients

cod liver oil (contains vitamins A+D), fragrance, light mineral oil, microcrystalline wax, paraffin

Questions?

Call 1-800-423-0139

Disclaimer

*This product is not manufactured or distributed by Bayer HealthCare LLC, distributor of A+D®Original Ointment.

Adverse Reactions

DISTRIBUTED BY TOPCO ASSOCIATES LLC,

ITASCA, IL 60143 1-888-423-0139

©TOPCO VIJA0923 tippytoesbrand.com

Scan here for more information or call 1-888-423-0139

Principal display panel

tippy toes®

COMPARE TO A+D® ORIGINAL OINTMENT*

baby vitamin a+d ointment

diaper rash ointment & skin protectant

- Prevents & Treats Diaper Rash
- Helps Heal Dry, Chafed Skin
- Hypoallergenic

NET WT 4 OZ (113 g)